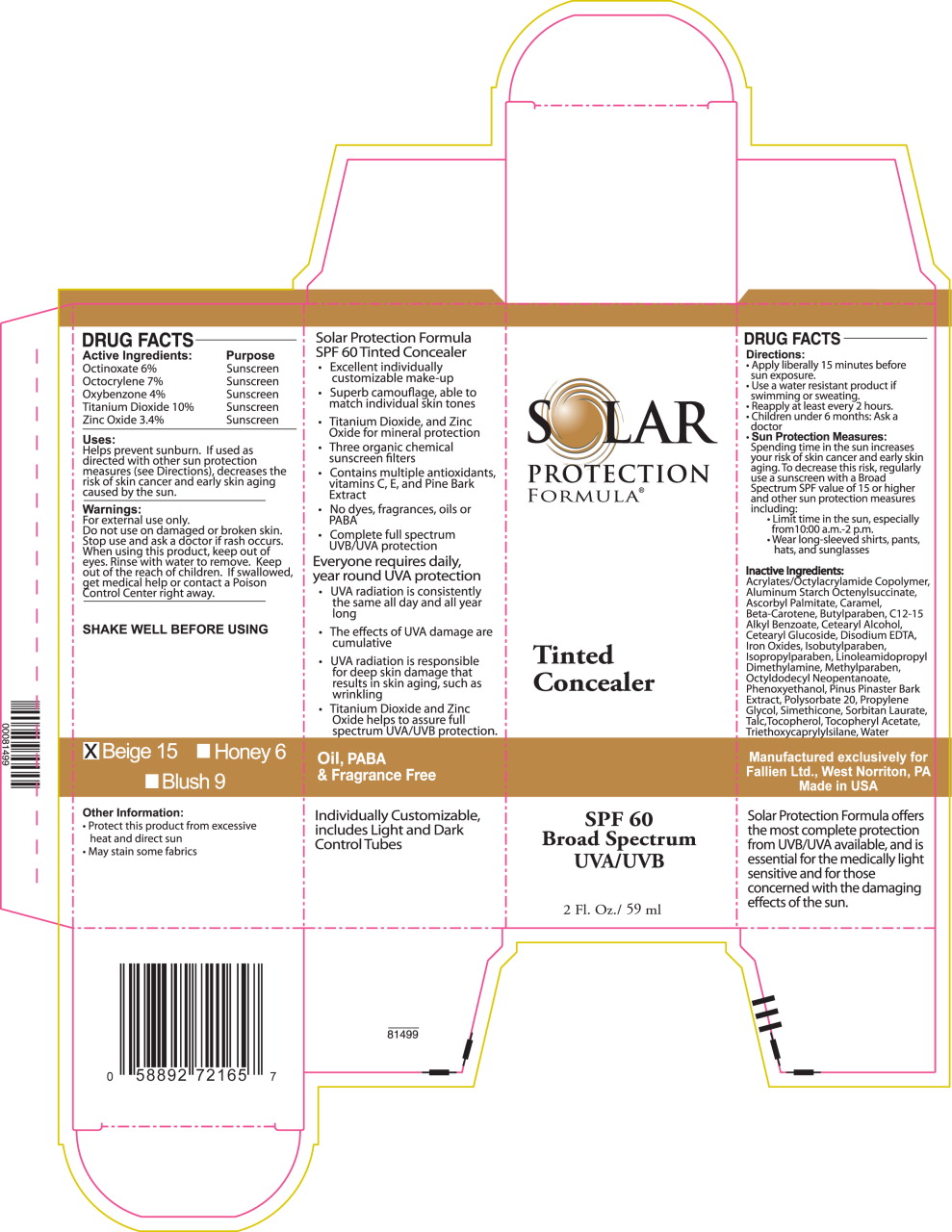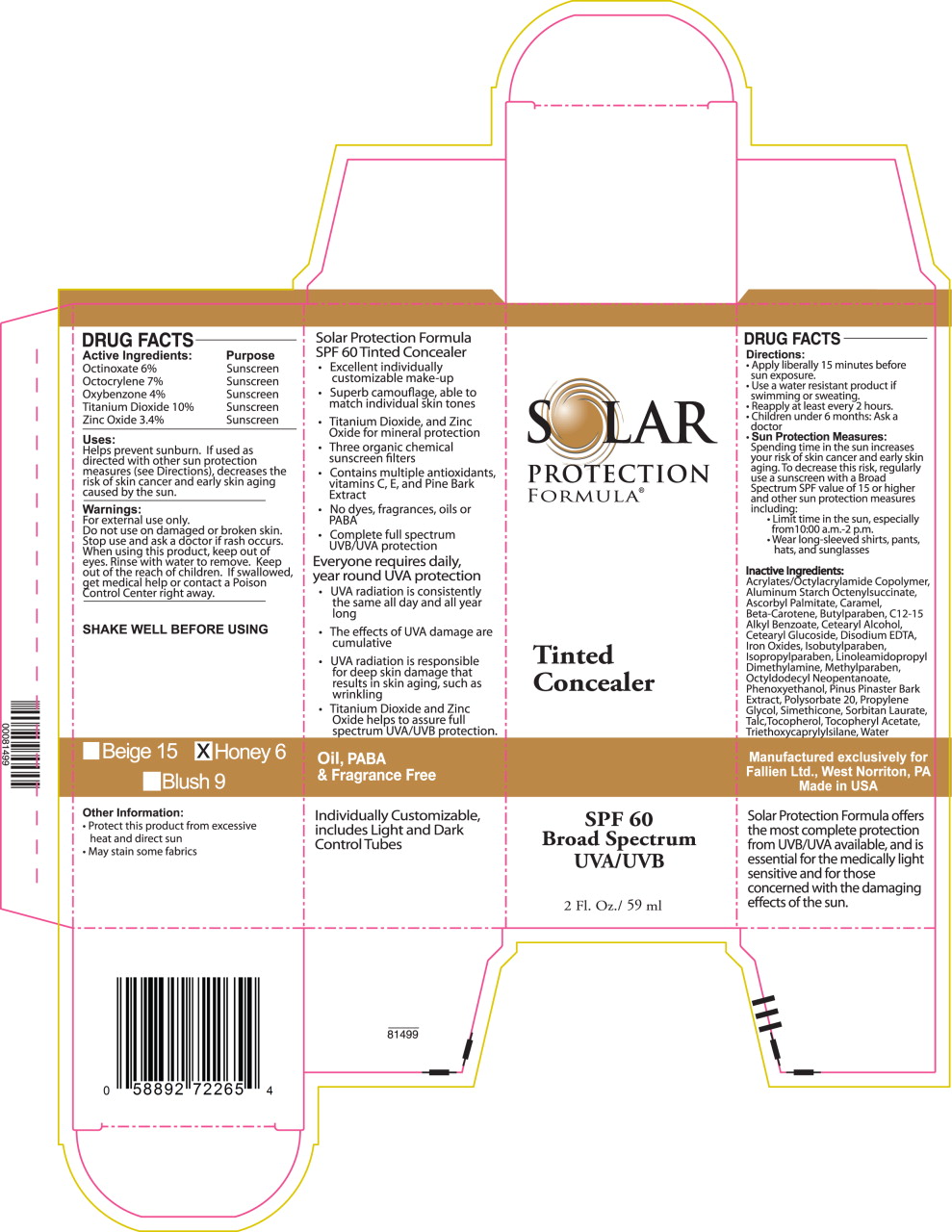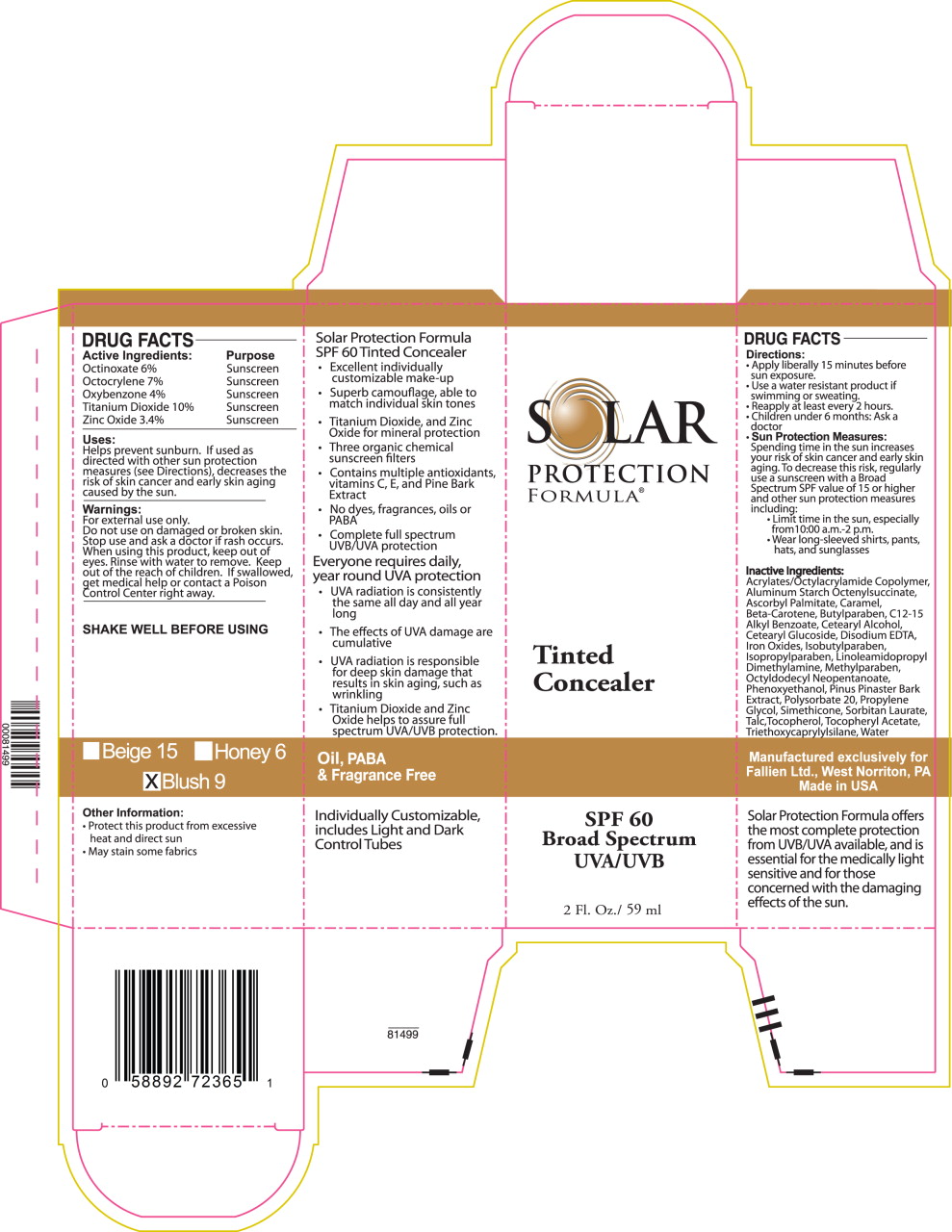 DRUG LABEL: Solar Protection Formula SPF 60 Tinted Concealer - (Beige) 
NDC: 58892-721 | Form: LOTION
Manufacturer: Fallien Cosmeceuticals, LTD.
Category: otc | Type: HUMAN OTC DRUG LABEL
Date: 20130114

ACTIVE INGREDIENTS: Octinoxate 69 mg/1 mL; Octocrylene 81 mg/1 mL; Oxybenzone 46 mg/1 mL; Titanium Dioxide 115 mg/1 mL; Zinc Oxide 39 mg/1 mL
INACTIVE INGREDIENTS: Alkyl (C12-15) Benzoate; Aluminum Starch Octenylsuccinate; Ascorbyl Palmitate; .BETA.-Carotene; Butylparaben; Caramel; Cetostearyl Alcohol; Cetearyl Glucoside; Dimethicone; Edetate Disodium; Ferric Oxide Red; Ferric Oxide Yellow; Ferrosoferric Oxide; Isobutylparaben; Isopropylparaben; Linoleamidopropyl Dimethylamine; Octyldodecyl Neopentanoate; Phenoxyethanol; Maritime Pine; Polysorbate 20; Propylene Glycol; Sorbitan Monolaurate; Talc; Tocopherol; .Alpha.-Tocopherol Acetate; Triethoxycaprylylsilane; Water

DRUG FACTS

Active Ingredients:

Octinoxate 6%

Octocrylene 7%

Oxybenzone 4%

Titanium Dioxide 10%

Zinc Oxide 3.4%

Purpose

Sunscreen

Sunscreen

Sunscreen

Sunscreen

Sunscreen

Uses:

Helps prevent sunburn. If used as directed with other sun protection measures (see Directions), decreases the risk of skin cancer and early skin aging caused by the sun.

Warnings:

For external use only.

Do not use on damaged or broken skin.

Stop use and ask a doctor if rash occurs.

When using this product, keep out of eyes. Rinse with water to remove.

KEEP OUT OF REACH OF CHILDREN

Keep out of the reach of children. If swallowed, get medical help or contact a Poison Control Center right away.

SHAKE WELL BEFORE USING

Other Information:

- Protect this product from excessive heat and direct sun
- May stain some fabrics

Directions:

- Apply liberally 15 minutes before sun exposure.
- Use a water resistant product if swimming or sweating.
- Reapply at least every 2 hours.
- Children under 6 months: Ask a doctor
- Sun Protection Measures:
  Spending time in the sun increases your risk of skin cancer and early skin aging. To decrease this risk, regularly use a sunscreen with a Broad Spectrum SPF value of 15 or higher and other sun protection measures including:
  - Limit time in the sun, especially from 10:00 a.m.-2 p.m.
  - Wear long-sleeved shirts, pants, hats, and sunglasses

Inactive Ingredients:

Acrylates/Octylacrylamide Copolymer, Aluminum Starch Octenylsuccinate, Ascorbyl Palmitate, Caramel, Beta-Carotene, Butylparaben, C12-15 Alkyl Benzoate, Cetearyl Alcohol, Cetearyl Glucoside, Disodium EDTA, Iron Oxides, Isobutylparaben, Isopropylparaben, Linoleamidopropyl Dimethylamine, Methylparaben, Octyldodecyl Neopentanoate, Phenoxyethanol, Pinus Pinaster Bark Extract, Polysorbate 20, Propylene Glycol, Simethicone, Sorbitan Laurate, Talc, Tocopherol, Tocopheryl Acetate, Triethoxycaprylylsilane, Water

Manufactured exclusively for Fallien Ltd., West Norriton, PA Made in USA

Solar Protection Formula offers the most complete protection from UVB/UVA available, and is essential for the medically light sensitive and for those concerned with the damaging effects of the sun.

Principal Display Panel – Beige Carton Label

SOLAR

PROTECTION

FORMULA®

TINTED
CONCEALER

SPF 60

Broad Spectrum

UVA/UVB

2 Fl.Oz./59 ml

Principal Display Panel – Honey Carton Label

SOLAR

PROTECTION

FORMULA®

TINTED
CONCEALER

SPF 60

Broad Spectrum

UVA/UVB

2 Fl.Oz./59 ml

Principal Display Panel – Blush Carton Label

SOLAR

PROTECTION

FORMULA®

TINTED
CONCEALER

SPF 60

Broad Spectrum

UVA/UVB

2 Fl.Oz./59 ml